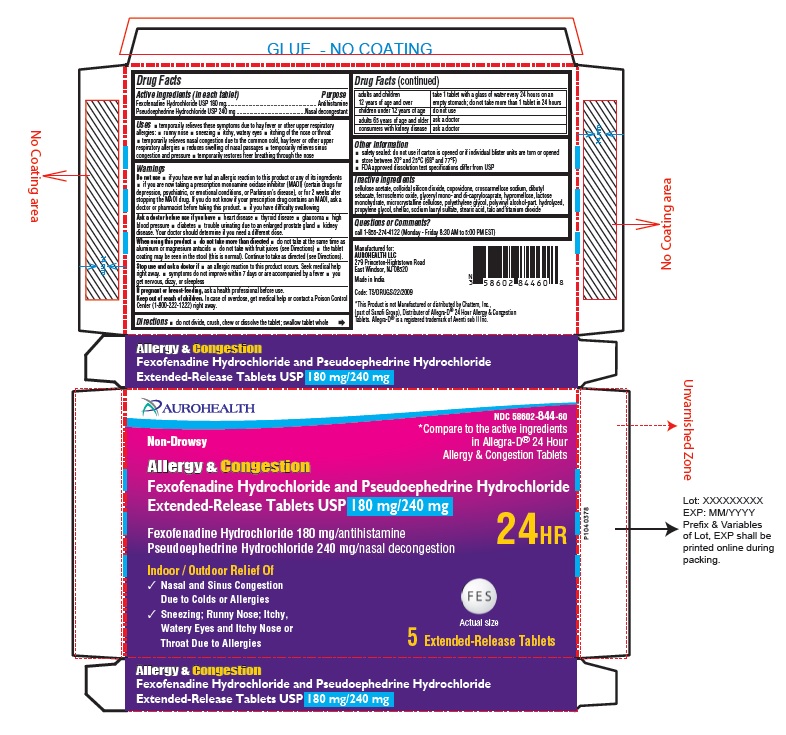 DRUG LABEL: Fexofenadine Hydrochloride and Pseudoephedrine Hydrochloride
NDC: 58602-844 | Form: TABLET, FILM COATED, EXTENDED RELEASE
Manufacturer: Aurohealth LLC
Category: otc | Type: Human OTC Drug Label
Date: 20250418

ACTIVE INGREDIENTS: FEXOFENADINE HYDROCHLORIDE 180 mg/1 1; PSEUDOEPHEDRINE HYDROCHLORIDE 240 mg/1 1
INACTIVE INGREDIENTS: CELLULOSE ACETATE; SILICON DIOXIDE; COPOVIDONE K25-31; CROSCARMELLOSE SODIUM; DIBUTYL SEBACATE; FERROSOFERRIC OXIDE; GLYCERYL MONO- AND DICAPRYLOCAPRATE; HYPROMELLOSE 2208 (100000 MPA.S); HYPROMELLOSE 2910 (3 MPA.S); LACTOSE MONOHYDRATE; MICROCRYSTALLINE CELLULOSE 200; POLYETHYLENE GLYCOL 400; POLYVINYL ALCOHOL, UNSPECIFIED; PROPYLENE GLYCOL; SHELLAC; SODIUM LAURYL SULFATE; STEARIC ACID; TALC; TITANIUM DIOXIDE

Fexofenadine Hydrochloride and Pseudoephedrine Hydrochloride Extended-Release Tablets USP

Drug Facts

Active ingredients (in each tablet)
Fexofenadine Hydrochloride USP 180 mg
Pseudoephedrine Hydrochloride USP 240 mg

Purpose

Antihistamine
Nasal decongestant

Uses

- temporarily relieves these symptoms due to hay fever or other upper respiratory allergies:
- runny nose
- sneezing
- itchy, watery eyes
- itching of the nose or throat
- temporarily relieves nasal congestion due to the common cold, hay fever or other upper respiratory allergies
- reduces swelling of nasal passages
- temporarily relieves sinus congestion and pressure
- temporarily restores freer breathing through the nose

Warnings

Do not use

- if you have ever had an allergic reaction to this product or any of its ingredients
- if you are now taking a prescription monoamine oxidase inhibitor (MAOI) (certain drugs for depression, psychiatric, or emotional conditions, or Parkinson’s disease), or for 2 weeks after stopping the MAOI drug. If you do not know if your prescription drug contains an MAOI, ask a doctor or pharmacist before taking this product.
- if you have difficulty swallowing

Ask a doctor before use if you have

- heart disease
- thyroid disease
- glaucoma
- high blood pressure
- diabetes
- trouble urinating due to an enlarged prostate gland
- kidney disease. Your doctor should determine if you need a different dose.

When using this product

- do not take more than directed
- do not take at the same time as aluminum or magnesium antacids
- do not take with fruit juices (see Directions)
- the tablet coating may be seen in the stool (this is normal). Continue to take as directed (see Directions).

Stop use and ask a doctor if

- an allergic reaction to this product occurs. Seek medical help right away.
- symptoms do not improve within 7 days or are accompanied by a fever
- you get nervous, dizzy, or sleepless

If pregnant or breast-feeding, ask a health professional before use.

Keep out of reach of children.

In case of overdose, get medical help or contact a Poison Control Center (1-800-222-1222) right away.

Directions

- do not divide, crush, chew or dissolve the tablet; swallow tablet whole

adults and children 12 years of age and over | take 1 tablet with a glass of water every 24 hours on an empty stomach; do not take more than 1 tablet in 24 hours
children under 12 years of age | do not use
adults 65 years of age and older | ask a doctor
consumers with kidney disease | ask a doctor

Other information

- safety sealed: do not use if carton is opened or if individual blister units are torn or opened
- store between 20° and 25°C (68° and 77°F)
- FDA approved dissolution test specifications differ from USP

Inactive ingredients

cellulose acetate, colloidal silicon dioxide, copovidone, croscarmellose sodium, dibutyl sebacate, ferrosoferric oxide, glyceryl mono- and di-caprylocaprate, hypromellose, lactose monohydrate, microcrystalline cellulose, polyethylene glycol, polyvinyl alcohol-part. hydrolyzed, propylene glycol, shellac, sodium lauryl sulfate, stearic acid, talc and titanium dioxide
Questions or Comments?
call 1-855-274-4122 (Monday - Friday 8:30 AM to 5:00 PM EST)
Manufactured for:
AUROHEALTH LLC
279 Princeton-Hightstown Road
East Windsor, NJ 08520
Made in India
Code: TS/DRUGS/22/2009

PACKAGE LABEL-PRINCIPAL DISPLAY PANEL - 1 x 5 Blister Carton

AUROHEALTH
NDC 58602-844-60
*Compare to the active ingredients
in Allegra-D® 24 Hour
Allergy & Congestion Tablets

Non-Drowsy

Allergy & Congestion
Fexofenadine Hydrochloride and Pseudoephedrine Hydrochloride
Extended-Release Tablets USP 180 mg/240 mg
Fexofenadine Hydrochloride 180 mg/antihistamine
Pseudoephedrine Hydrochloride 240 mg/nasal decongestion
24 HR
Indoor / Outdoor Relief Of

- Nasal and Sinus Congestion Due to Colds or Allergens
- Sneezing; Runny Nose; Itchy, Watery Eyes and Itchy Nose or Throat Due to Allergies

Actual size
5 Extended-Release Tablets